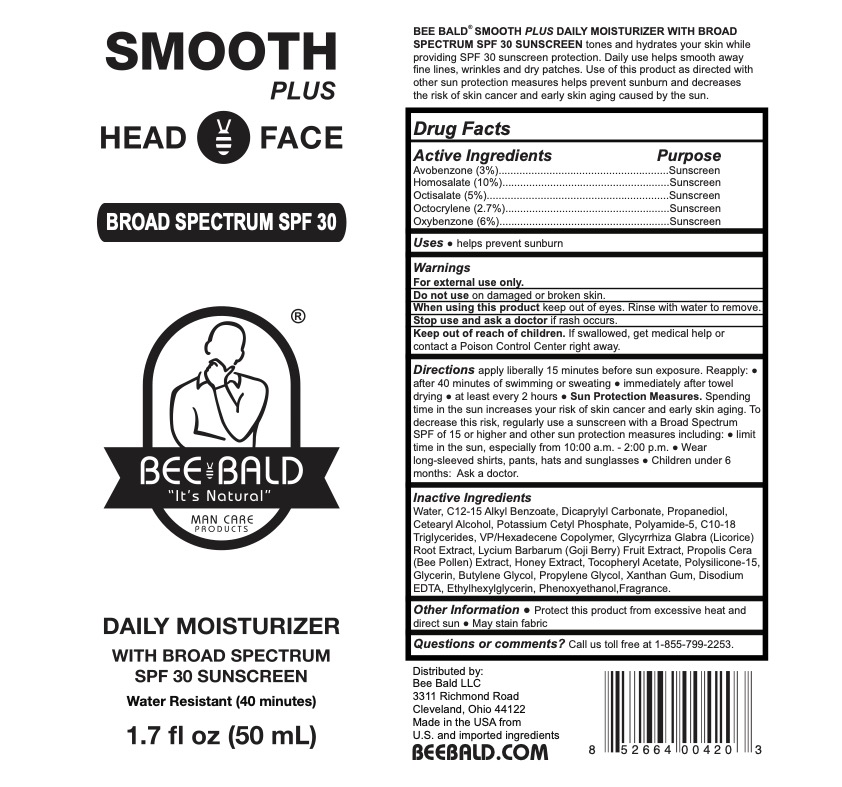 DRUG LABEL: Bee Bald Smooth Plus Daily Moisturizer SPF 30 Sunscreen
NDC: 72839-138 | Form: LOTION
Manufacturer: Derma Care Research Labs, LLC
Category: otc | Type: HUMAN OTC DRUG LABEL
Date: 20241219

ACTIVE INGREDIENTS: OXYBENZONE 6 g/100 mL; OCTISALATE 5 g/100 mL; HOMOSALATE 10 g/100 mL; OCTOCRYLENE 2.7 g/100 mL; AVOBENZONE 3 g/100 mL
INACTIVE INGREDIENTS: XANTHAN GUM; POTASSIUM CETYL PHOSPHATE; LYCIUM BARBARUM FRUIT; PROPYLENE GLYCOL; DICAPRYLYL CARBONATE; BEE POLLEN; CETOSTEARYL ALCOHOL; POLYAMIDE-5; VINYLPYRROLIDONE/HEXADECENE COPOLYMER; ALKYL (C12-15) BENZOATE; PROPANEDIOL; BUTYLENE GLYCOL; EDETATE DISODIUM; C10-18 TRIGLYCERIDES; HONEY; POLYSILICONE-15; ETHYLHEXYLGLYCERIN; WATER; PHENOXYETHANOL; .ALPHA.-TOCOPHEROL ACETATE; LICORICE; GLYCERIN

Bee Bald Smooth Plus Daily Moisturizer SPF 30 Sunscreen Lotion

Active Ingredients

Avobenzone 3%, Homosalate 10%, Octisalate 5%, Octocrylene 2.7%, Oxybenzone 6%

Purpose

Sunscreen

Uses

Helps prevent sunburn.

Warnings

For external use only.

Do not use on damaged or broken skin. When using this product keep out of eyes. Rinse eyes with water to remove.

Stop use and ask a doctor if rash occurs.

Keep Out of Reach of Children.

If swallowed, get medical help or contact a Poison Control Center right away.

Directions

Apply liberally 15 minutes before sun exposure. Reapply:

- after 40 minutes of swimming or sweating
- immediately after towel drying
- at least every 2 hours

Sun protection measures: spending time in the sun increases your risk of skin cancer and early skin aging. To decrease risk, regularly use a sunscreen with broad spectrum SPF of 15 or higher and other sun protection measures including:

- limit time in the sun, especially from 10 am to 2 pm
- wear long-sleeved shirts, pants, hats, and sunglasses.
- Children under 6 months: ask a doctor.

Inactive Ingredients

Water, C12-15 Alkyl Benzoate, Dicaprylyl Carbonate, Propanediol, Cetearyl Alcohol, Potassium Cetyl Phosphate, Polyamide-5, C10-18 Triglycerides, VP/Hexadecene Copolymer, Glycyrrhiza Glabra (Licorice) Root Extract, Lycium Barbarum (Goji Berry) Fruit Extract, Propolis Cera (Bee Pollen) Extract, Honey Extract, Tocopheryl Acetate, Polysilicone-15, Glycerin, Butylene Glycol, Propylene Glycol, Xanthan Gum, Disodium EDTA, Ethylhexylglycerin, Phenoxyethanol, Fragrance.